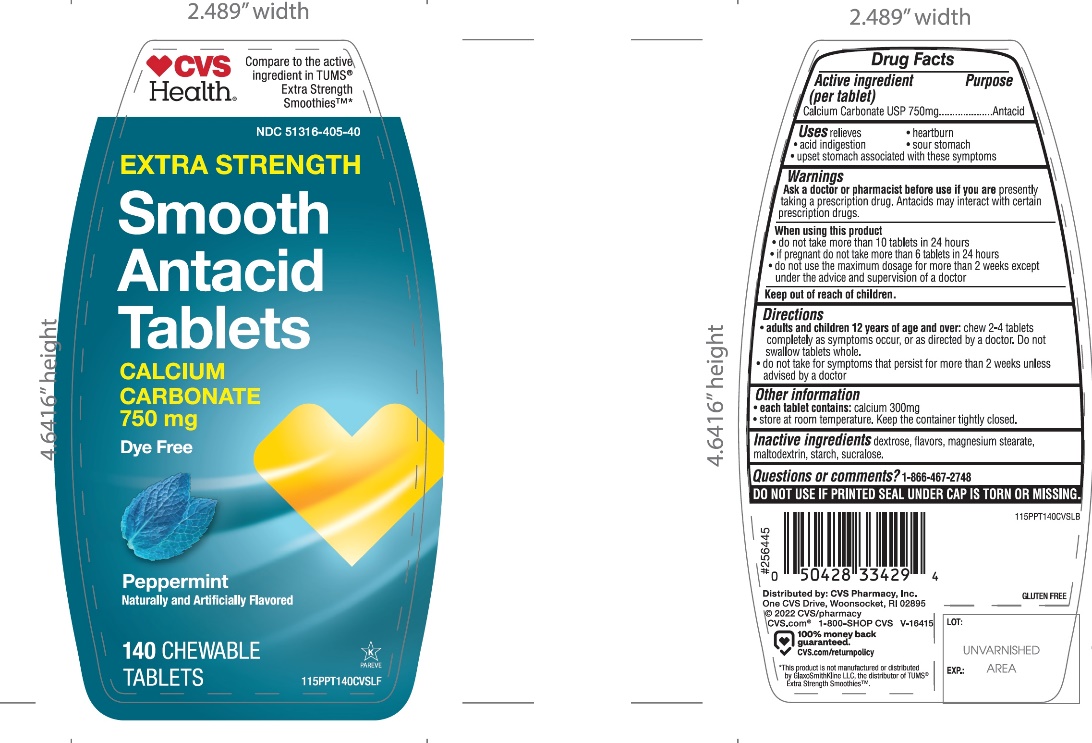 DRUG LABEL: CVS

NDC: 51316-405 | Form: TABLET, CHEWABLE
Manufacturer: CVS PHARMACY
Category: otc | Type: HUMAN OTC DRUG LABEL
Date: 20251208

ACTIVE INGREDIENTS: CALCIUM CARBONATE 750 mg/1 1
INACTIVE INGREDIENTS: DEXTROSE, UNSPECIFIED FORM; MAGNESIUM STEARATE; MALTODEXTRIN; STARCH, CORN; SUCRALOSE

CVS Extra Strength Smooth Antacid 140 Chewable Tablets

Active ingredient (per tablet)

Calcium Carbonate USP 750mg

Purpose

Antacid

Uses

relieves

- heartburn
- acid indigestion
- sour stomach
- upset stomach associated with these symptoms

Warnings

Ask a doctor or pharmacist before use if you arepresently taking a prescription drug. Antacids may interact with certain prescription drugs.

When using this product

- do not take more than 10 tablets in 24 hours
- if pregnant do not take more than 6 tablets in 24 hours
- do not use the maximum dosage for more than 2 weeks except under the advice and supervision of a doctor.

Directions

- adults and children 12 years of age and over:chew 2-4 tablets completely as symptoms occur, or as directed by a doctor. Do not swallow tablets whole.
- do not take for symptoms that persist for more than 2 weeks unless advised by a doctor

Other information

- each tablet contains:elemental calcium 300mg
- store at room temperature. Keep the container tightly closed

Inactive ingredients

dextrose, flavors, magnesium stearate, maltodextrin, starch, sucralose,

Safety sealed: DO NOT USE IF PRINTED SEAL UNDER CAP IS TORN OR MISSING

Questions

1-866-467-2748

Package/Label Principal Display Panel

Compare to active ingredient in Extra Strength TUMS®Smoothies™

Extra Strength

Smooth Antacid Tablets

Calcium carbonate, 750 mg

DYE FREE

Fast Relief of Upset Stomach, Heartburn, and Acid Indigestion

Peppermint

GLUTEN-FREE

Distributed by:

*This product is not manufactured or distributed by GlaxoSmithKline LLC, distributor of Extra Strength Tums® Smoothies™.